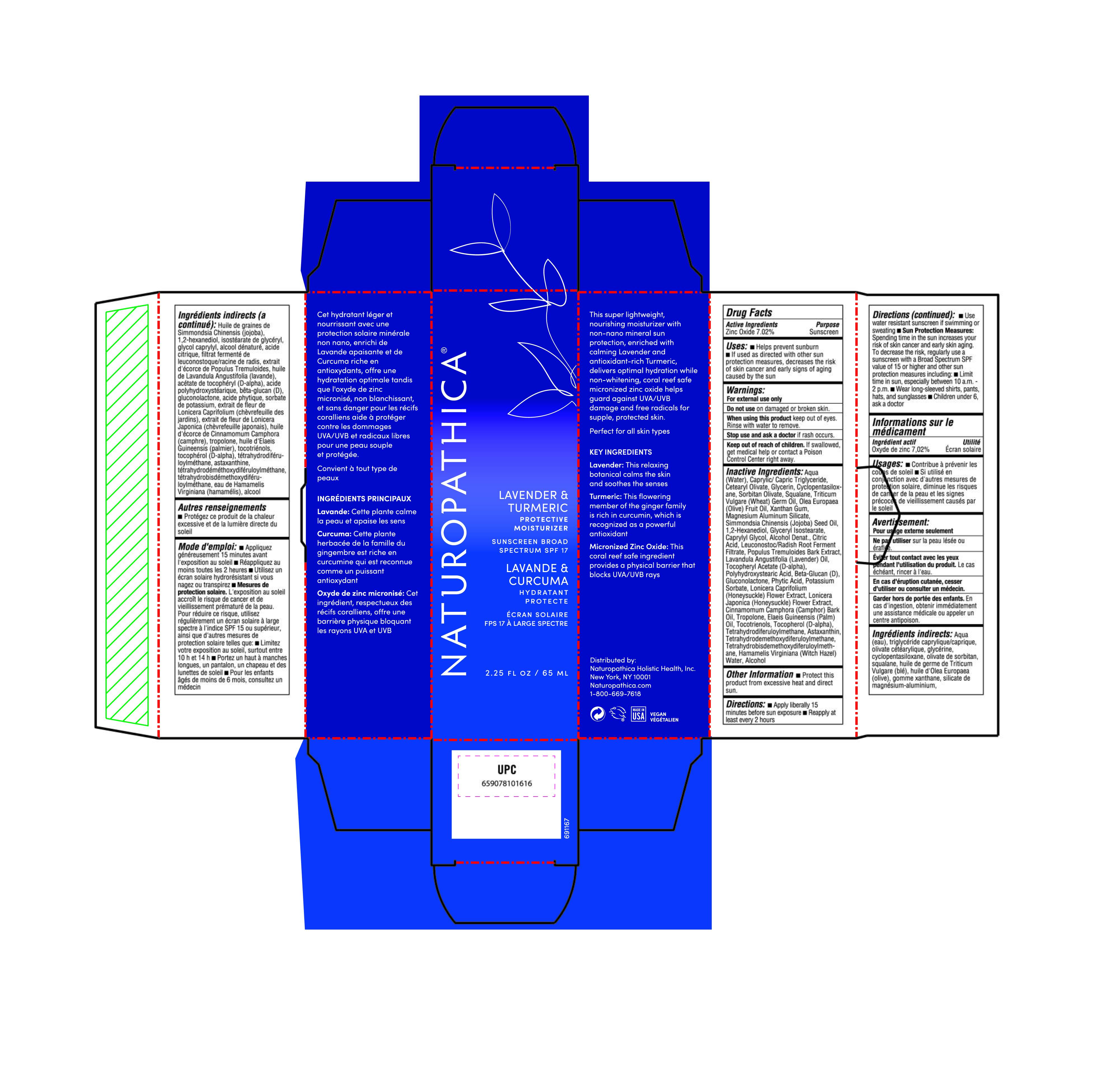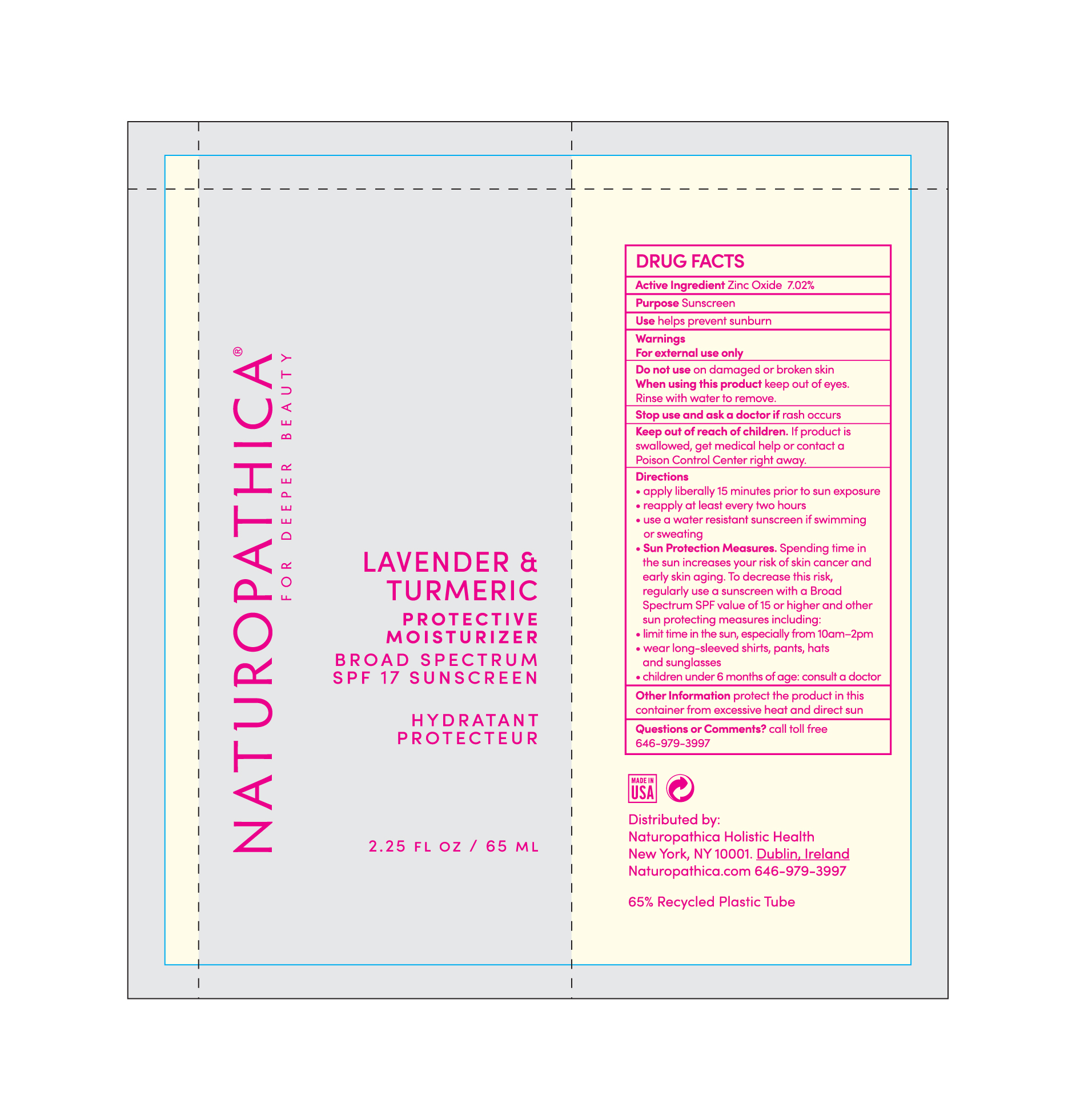 DRUG LABEL: Lavender Protective Moisturizer SPF 17
NDC: 64657-006 | Form: LOTION
Manufacturer: Naturopathica Holistic Health, Inc.
Category: otc | Type: HUMAN OTC DRUG LABEL
Date: 20240523

ACTIVE INGREDIENTS: ZINC OXIDE 7.02 g/100 mL
INACTIVE INGREDIENTS: TETRAHYDRODEMETHOXYDIFERULOYLMETHANE; FYTIC ACID; POPULUS TREMULOIDES BARK; LAVENDER OIL; WATER; WHEAT GERM OIL; TETRAHYDRODIFERULOYLMETHANE; XANTHAN GUM; MEDIUM-CHAIN TRIGLYCERIDES; GLYCERIN; CYCLOMETHICONE 5; CETEARYL OLIVATE; SORBITAN OLIVATE; OLEA EUROPAEA (OLIVE) OIL UNSAPONIFIABLES; SQUALANE; MAGNESIUM ALUMINUM SILICATE; JOJOBA OIL; GLYCERYL ISOSTEARATE; CAPRYLYL GLYCOL; LEUCONOSTOC/RADISH ROOT FERMENT FILTRATE; POTASSIUM SORBATE; LONICERA JAPONICA FLOWER; .ALPHA.-TOCOPHEROL ACETATE, DL-; TOCOTRIENOLS; .ALPHA.-TOCOPHEROL, D-; ASTAXANTHIN; HAMAMELIS VIRGINIANA FLOWER WATER; GLUCONOLACTONE; LONICERA CAPRIFOLIUM FLOWER; YEAST .BETA.-D-GLUCAN; CAMPHOR OIL; TETRAHYDROBISDEMETHOXYDIFERULOYLMETHANE; ALCOHOL; PALM OIL; 1,2-HEXANEDIOL; CITRIC ACID ACETATE; POLYHYDROXYSTEARIC ACID (2300 MW)

Active Ingredient

Zinc Oxide 7.02%

Purpose

Sunscreen

Uses

• Helps prevent sunburn

• If used as directed with other sun protection measures (see Directions), decreases the risk of skin cancer and early signs of aging caused by the sun

Warning

• For external use only.

• Do not use on damaged or broken skin.

• When using this product keep out of eyes. Rinse with water to remove.

• Stop use and ask a doctor if rash occurs.

Keep out of reach of children. If swallowed, get medical help or contact a Poison Control Center right away.

Inactive Ingredients

Aqua (Water), Caprylic/ Capric Triglyceride, Cetearyl Olivate, Glycerin, Cyclopentasiloxane, Sorbitan olivate, Squalane, Triticum Vulgare (Wheat) Germ Oil, Olea Europaea (Olive) Fruit Oil, Xanthan Gum, Magnesium Aluminum Silicate, Simmondsia Chinensis (Jojoba) Seed Oil, 12-Hexanediol, Glyceryl lsostearate, Caprylyl Glycol, Alcohol Denat., Citric Acid, Leuconostoc/Radish Root Ferment Filtrate, Populus Tremuloides Bark Extract, Lavandula Angustifolia (Lavender) Oil, Tocopheryl Acetate (D-alpha), Polyhydroxystearic Acid, Beta-Glucan (D), Gluconolactone, Phytic Acid, Potassium Sorbate, Lonicera Caprifolium (Honeysuckle) Flower Extract, Lonicera Japonica (Honeysuckle) Flower Extract, Cinnamomum Camphora (Camphor) Bark Oil, Tropolone, Elaeis Guineensis (Palm) oil, Tocotrienols, Tocopherol (D-alpha), Tetrahydrodiferuloylmethane, Astaxanthin, Tetrahydrodemethoxydiferuloylmethane, Tetrahydrobisdemethoxydiferuloylmethane, Hamamelis Virginiana (Witch Hazel) Water, Alcohol,

Other information

Protect the product in this container from excessive heat and direct sun

Directions

• Apply liberally 15 minutes before sun exposure

• Reapply at least every 2 hours

• Use water resistant sunscreen if swimming or sweating

• Sun Protection Measures: Spending time in the sun increases your risk of skin cancer and early skin aging. To decrease the risk, regularly use a sunscreen with a Broad Spectrum SPF value of 15 or higher and other sun protection measures including:

• Limit lime in sun, especially between 10 a.m. - 2 p.m.

• Wear long-sleeved shirts, pants, hats, and sunglasses

• Children under 6, ask a doctor